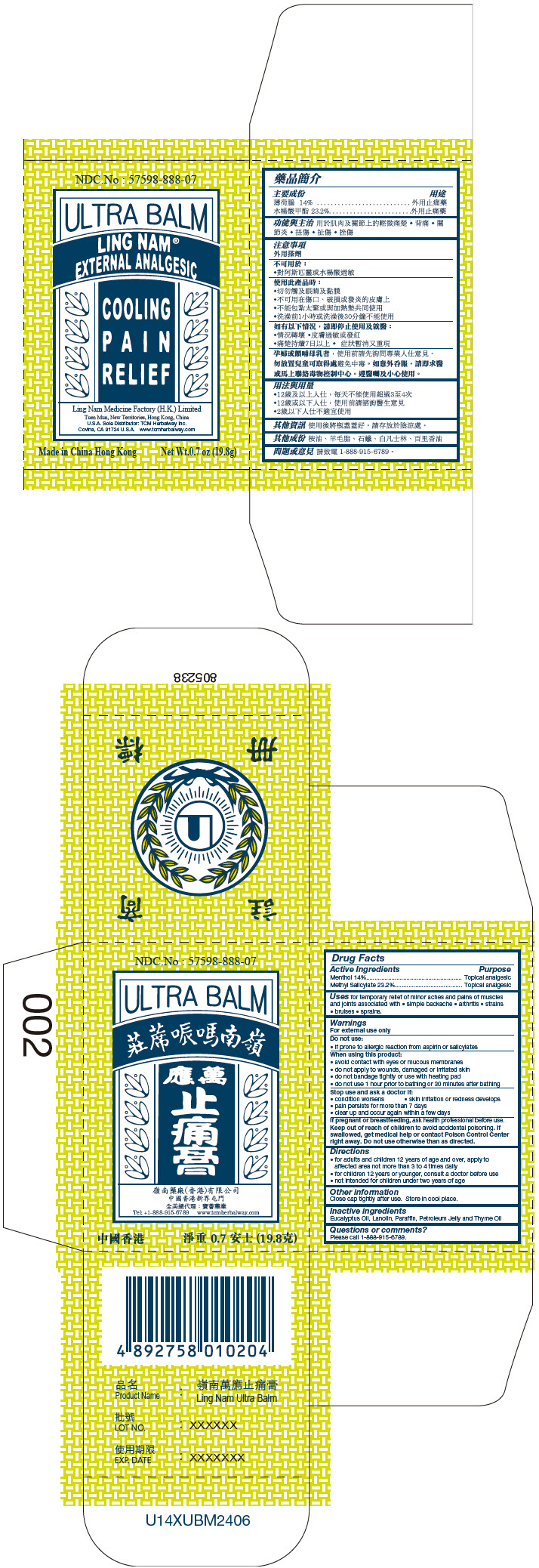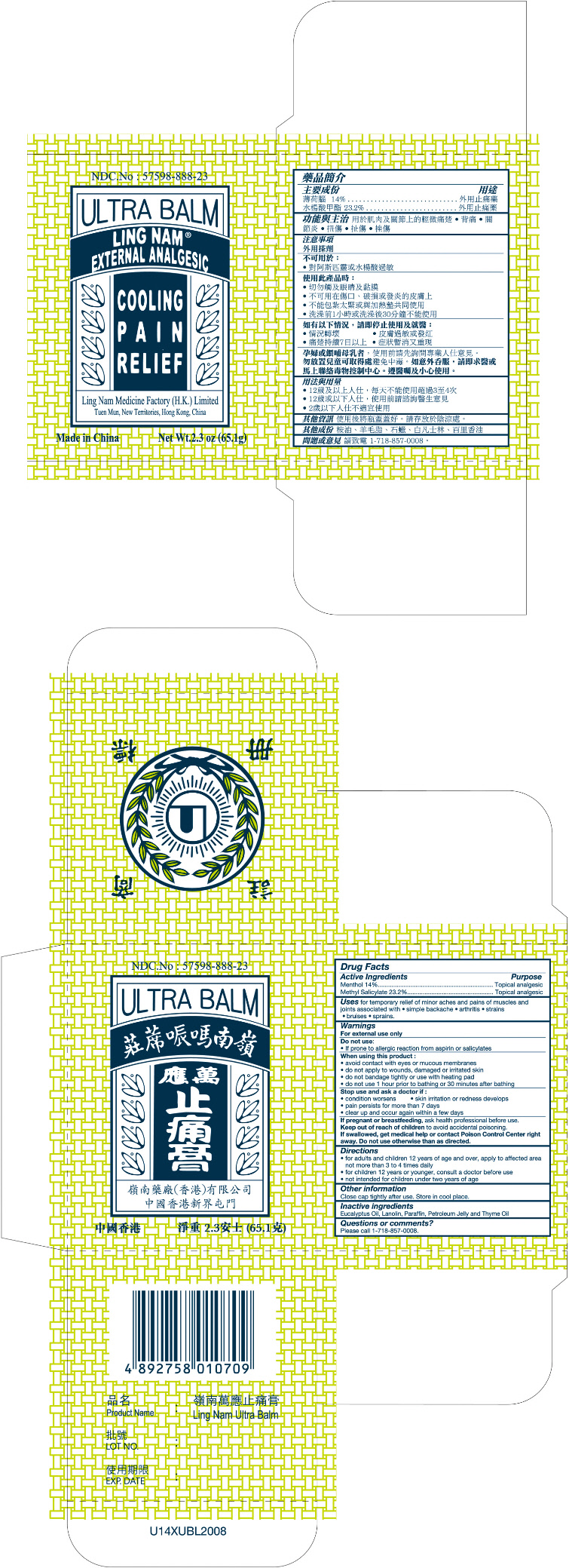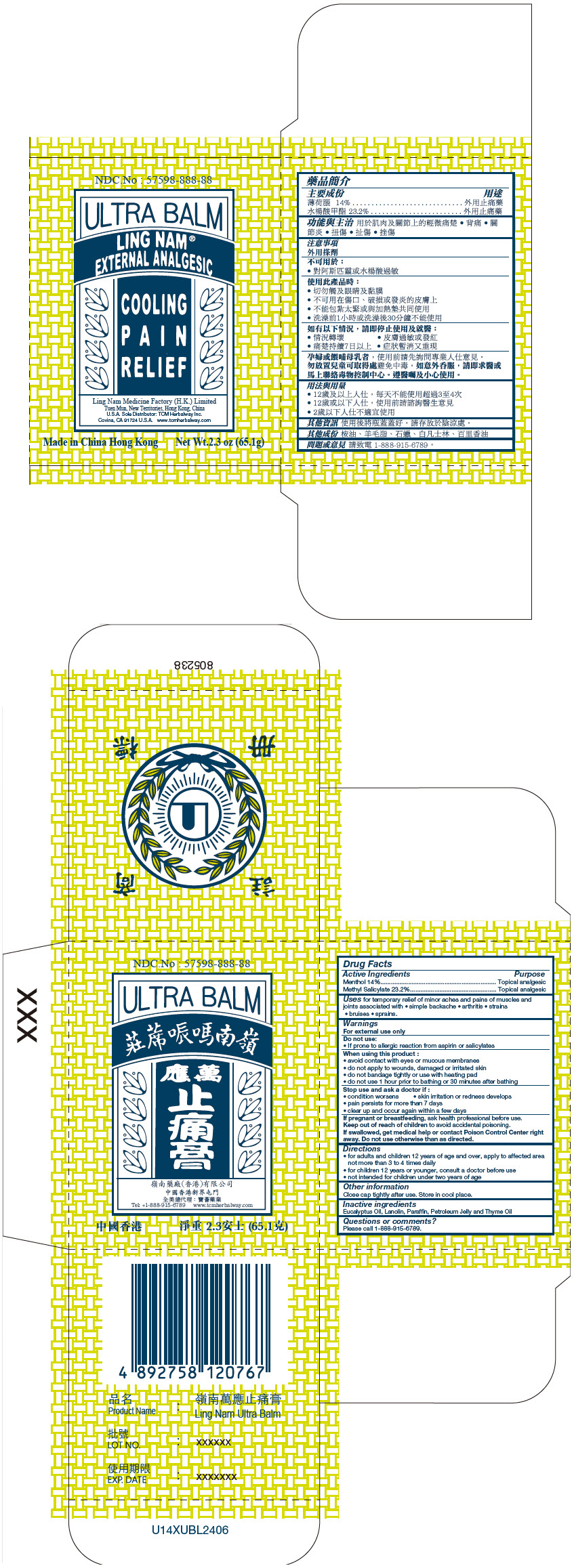 DRUG LABEL: Ultra Balm
NDC: 57598-888 | Form: OINTMENT
Manufacturer: Ling Nam Medicine Factory (H.K.) Ltd.
Category: otc | Type: HUMAN OTC DRUG LABEL
Date: 20240719

ACTIVE INGREDIENTS: Menthol, Unspecified Form 140 mg/1 g; Methyl Salicylate 232 mg/1 g
INACTIVE INGREDIENTS: Eucalyptus Oil; Lanolin; Paraffin; Petrolatum; Thyme Oil

Ultra Balm

Drug Facts

ACTIVE INGREDIENT

Active Ingredients | Purpose
Menthol 14% | Topical analgesic
Methyl Salicylate 23.2% | Topical analgesic

Uses

for temporary relief of minor aches and pains of muscles and joints associated with

- simple backache
- arthritis
- strains
- bruises
- sprains

Warnings

For external use only

Do not use

- If prone to allergic reaction from aspirin or salicylates

When using this product

- avoid contact with eyes or mucous membranes
- do not apply to wounds, damaged or irritated skin
- do not bandage tightly or use with heating pad
- do not use 1 hour prior to bathing or 30 minutes after bathing

Stop use and ask a doctor if

- condition worsens
- skin irritation or redness develops
- pain persists for more than 7 days
- clear up and occur again within a few days

PREGNANCY OR BREAST FEEDING

If pregnant or breastfeeding, ask health professional before use.

Keep out of reach of children to avoid accidental poisoning. If swallowed, get medical help or contact Poison Control Center right away. Do not use otherwise than as directed.

Directions

- for adults and children 12 years of age and over, apply to affected area not more than 3 to 4 times daily
- for children 12 years or younger, consult a doctor before use
- not intended for children under two years of age

Other information

Close cap tightly after use. Store in cool place.

Inactive ingredients

Eucalyptus Oil, Lanolin, Paraffin, Petroleum Jelly and Thyme Oil

Questions or comments?

Please call 1-888-915-6789.

PRINCIPAL DISPLAY PANEL - 19.8 g Jar Carton

NDC.No : 57598-888-07

ULTRA BALM

LING NAM®
EXTERNAL ANALGESIC

COOLING
PAIN
RELIEF

Ling Nam Medicine Factory (H.K.) Limited
Tuen Mun, New Territories, Hong Kong, China
U.S.A. Sole Distributor: TCM Herbalway Inc.
Covina, CA 91724 U.S.A. www.tcmherbalway.com

Made in China Hong Kong
Net Wt.0.7 oz (19.8g)

PRINCIPAL DISPLAY PANEL - 65.1 g Jar Carton

NDC.No : 57598-888-23

ULTRA BALM

LING NAM®
EXTERNAL ANALGESIC

COOLING
PAIN
RELIEF

Ling Nam Medicine Factory (H.K.) Limited
Tuen Mun, New Territories, Hong Kong, China

Made in China
Net Wt.2.3 oz (65.1g)

PRINCIPAL DISPLAY PANEL - 65.1 g Jar Carton - NDC 57598-888-88

NDC.No : 57598-888-88

ULTRA BALM

LING NAM®
EXTERNAL ANALGESIC

COOLING
PAIN
RELIEF

Ling Nam Medicine Factory (H.K.) Limited
Tuen Mun, New Territories, Hong Kong, China
U.S.A. Sole Distributor: TCM Herbalway Inc.
Covina, CA 91724 U.S.A. www.tcmherbalway.com

Made in China Hong Kong
Net Wt.2.3 oz (65.1g)